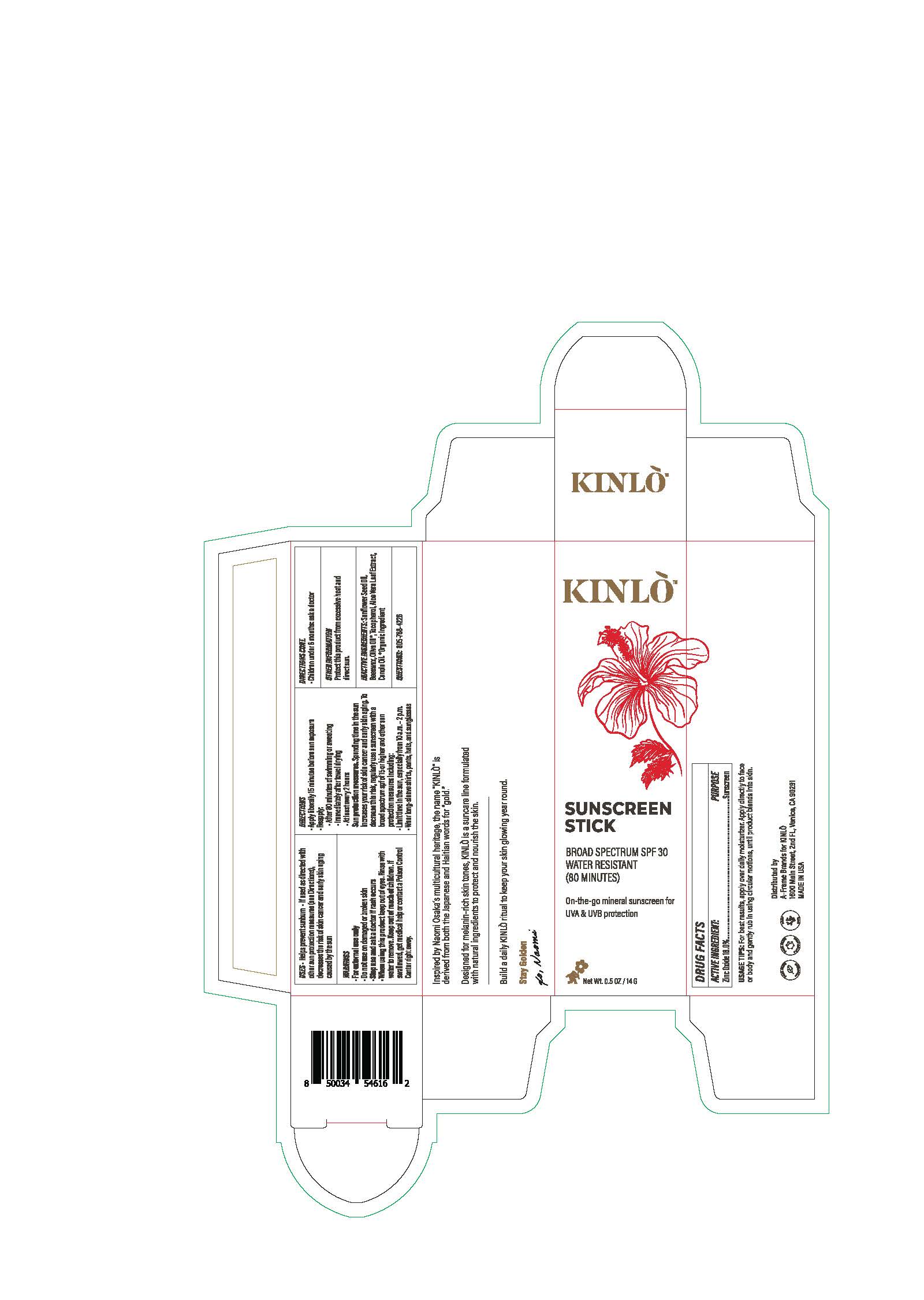 DRUG LABEL: Kinlo Sunscreen Stick Broad Spectrum SPF 30
NDC: 82184-5140 | Form: STICK
Manufacturer: A-frame Sunco Inc
Category: otc | Type: HUMAN OTC DRUG LABEL
Date: 20220226

ACTIVE INGREDIENTS: ZINC OXIDE 18 g/100 g
INACTIVE INGREDIENTS: ALOE VERA LEAF; SYNTHETIC BEESWAX; CANOLA OIL; HELIANTHUS ANNUUS SEED WAX; OLEA EUROPAEA FRUIT VOLATILE OIL; TOCOPHEROL

DRUG FACTS

Active Ingredients

Zinc Oxide 18%

Uses

• helps prevent sunburn • if used as directed with other
sun protection measures (see Directions), decreases the
risk of skin cancer and early skin aging caused by the sun

Warnings

For external use only
Do not use on damaged or broken skin
When using this product keep out of eyes. Rinse with water to remove.
Stop use and ask a docor if rash occurs
Keep out of reach of children. If swalled, get medical help or contact a Poison Control Center right away.

Directions

• apply liberally 15 minutes before sun exposure
• reapply:
• after 80 minutes of swimming or sweating
• immediately after towel drying
• at least every 2 hours
• Sun Protection Measures. Spending time in the sun increases your risk
of skin cancer and early skin aging. To decrease this risk, regularly use
a sunscreen with a broad spectrum SPF of 15 or higher and other sun
protection measures including:
• limit time in the sun, especially from 10 a.m. – 2 p.m.
• wear long-sleeve shirts, pants, hats, and sunglasses
• children under 6 months: Ask a doctor

Inactive ingredients

Aloe Barbadensis (Aloe Vera) Leaf Extract, Beeswax, Canola Oil, Helianthus Annuus (Sunflower) Seed Oil, Olea Europaea (Olive) Fruit Oil, Tocopherol

Other Information

• protect the product in this container from excessive
heat and direct sun